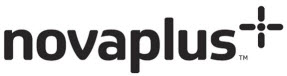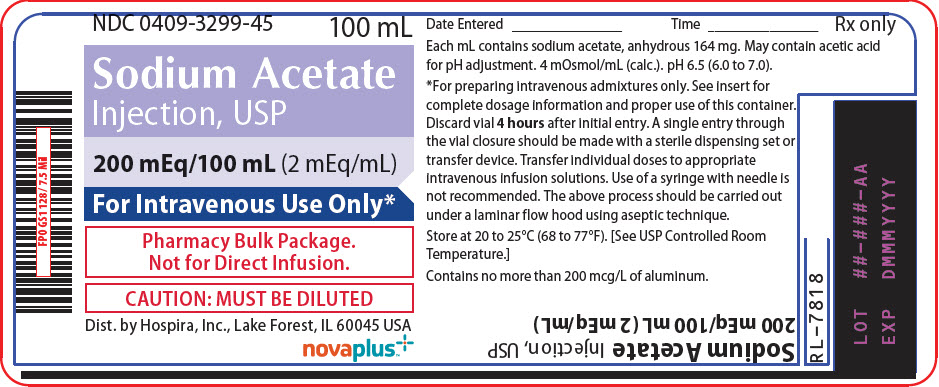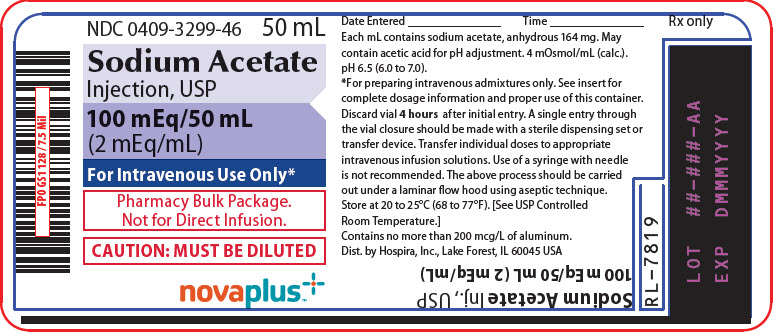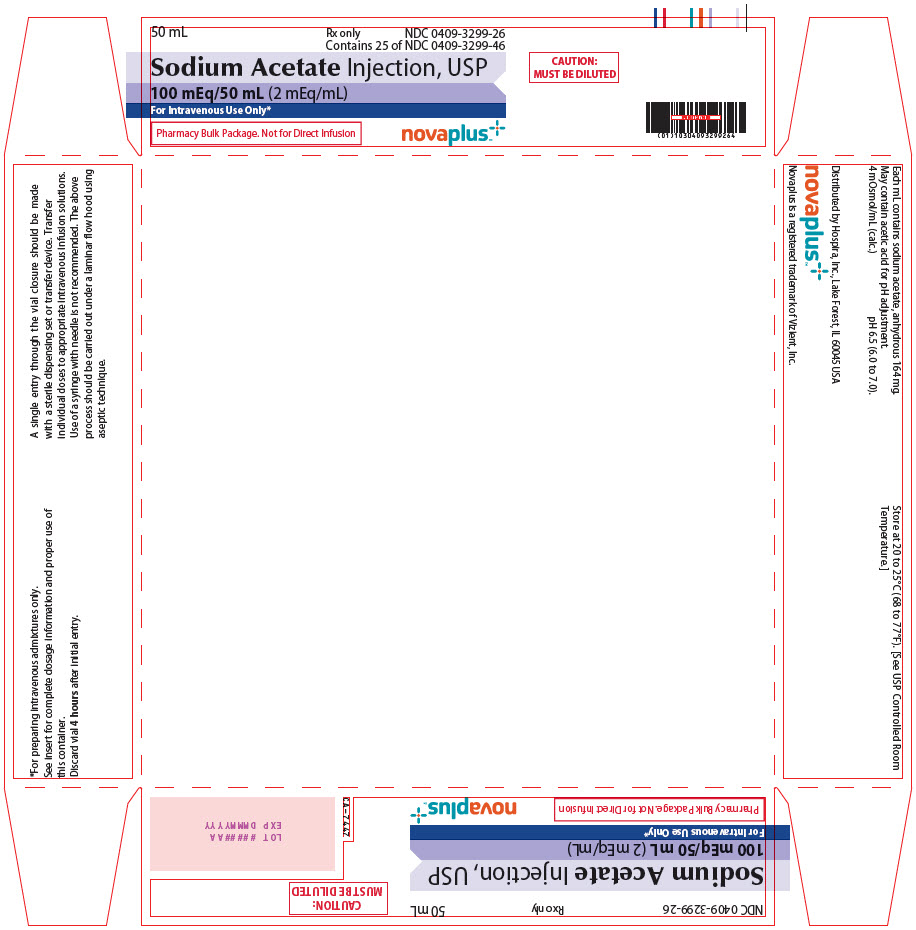 DRUG LABEL: Sodium Acetate
NDC: 0409-3299 | Form: INJECTION, SOLUTION, CONCENTRATE
Manufacturer: Hospira, Inc.
Category: prescription | Type: HUMAN PRESCRIPTION DRUG LABEL
Date: 20241108

ACTIVE INGREDIENTS: SODIUM ACETATE ANHYDROUS 164 mg/1 mL
INACTIVE INGREDIENTS: ACETIC ACID; WATER

SODIUM ACETATE Rx only

Injection, USP

2 mEq/mL

Pharmacy Bulk Package.

Not for Direct Infusion

FOR ADDITIVE USE ONLY AFTER DILUTION IN INTRAVENOUS FLUIDS.

Glass Fliptop Vial

DESCRIPTION

Sodium Acetate Injection, USP (2 mEq/mL) is a sterile, nonpyrogenic, concentrated solution of sodium acetate in water for injection. The solution is administered after dilution by the intravenous route as an electrolyte replenisher. It must not be administered undiluted. Each mL contains 164 mg of sodium acetate (anhydrous) which provides 2 mEq each of sodium (Na^+) and acetate (CH3COO^-). The solution contains no bacteriostat, antimicrobial agent or added buffer. May contain acetic acid for pH adjustment; the pH is 6.5 (6.0 to 7.0). The osmolar concentration is 4 mOsmol/mL (calc.); specific gravity 1.081.

The solution is intended as an alternative to sodium chloride to provide sodium ion (Na^+) for addition to large volume infusion fluids for intravenous use.

Sodium Acetate, USP anhydrous is chemically designated CH3COONa, a hygroscopic powder very soluble in water.

A Pharmacy Bulk Package is a container of a sterile preparation for parenteral use that contains many single doses. The contents are intended for use in a pharmacy admixture program and are restricted to the preparation of admixtures for intravenous infusion.

CLINICAL PHARMACOLOGY

Sodium is the principal cation of extracellular fluid. It comprises more than 90% of total cations at its normal plasma concentration of approximately 140 mEq/liter. The sodium ion exerts a primary role in controlling total body water and its distribution.

Acetate (CH3COO^-) is a hydrogen ion acceptor. It also serves as an alternate source of bicarbonate (HCO3^-) by metabolic conversion in the liver. This conversion has been shown to proceed readily, even in the presence of severe liver disease.

INDICATIONS AND USAGE

Sodium Acetate Injection, USP (2 mEq/mL) is indicated as a source of sodium for addition to large volume intravenous fluids to prevent or correct hyponatremia in patients with restricted or no oral intake. It is also useful as an additive for preparing specific intravenous fluid formulas when the needs of the patient cannot be met by standard electrolyte or nutrient solutions.

CONTRAINDICATIONS

Sodium Acetate Injection, USP (2 mEq/mL) is contraindicated in patients with hypernatremia or fluid retention.

WARNINGS

Sodium Acetate Injection, USP (2 mEq/mL) must be diluted before use.

To avoid sodium overload and water retention, infuse sodium-containing solutions slowly.

Solutions containing sodium ions should be used with great care, if at all, in patients with congestive heart failure, severe renal insufficiency and in clinical states in which there exists edema with sodium retention.

In patients with diminished renal function, administration of solutions containing sodium ions may result in sodium retention.

Solutions containing acetate ions should be used with great care in patients with metabolic or respiratory alkalosis. Acetate should be administered with great care in those conditions in which there is an increased level or an impaired utilization of this ion, such as severe hepatic insufficiency.

The intravenous administration of this solution (after appropriate dilution) can cause fluid and/or solute overloading resulting in dilution of other serum electrolyte concentrations, overhydration, congested states or pulmonary edema. Excessive administration of potassium free solutions may result in significant hypokalemia.

WARNING: This product contains aluminum that may be toxic. Aluminum may reach toxic levels with prolonged parenteral administration if kidney function is impaired. Premature neonates are particularly at risk because their kidneys are immature, and they require large amounts of calcium and phosphate solutions, which contain aluminum.

Research indicates that patients with impaired kidney function, including premature neonates, who receive parenteral levels of aluminum at greater than 4 to 5 mcg/kg/day accumulate aluminum at levels associated with central nervous system and bone toxicity. Tissue loading may occur at even lower rates of administration.

PRECAUTIONS

Do not administer unless solution is clear and seal is intact. Discard unused portion.

Sodium replacement therapy should be guided primarily by the serum sodium level.

Caution should be exercised in administering sodium-containing solutions to patients with severe renal function impairment, cirrhosis, cardiac failure, or other edematous or sodium-retaining states, as well as in patients with oliguria or anuria.

Caution must be exercised in the administration of parenteral fluids, especially those containing sodium ions, to patients receiving corticosteroids or corticotropin.

Solutions containing acetate ions should be used with caution as excess administration may result in metabolic alkalosis.

Pregnancy: Animal reproduction studies have not been conducted with Sodium Acetate Injection, USP. It is also not known whether Sodium Acetate Injection, USP can cause fetal harm when administered to a pregnant woman or can affect reproduction capacity. Sodium Acetate Injection, USP should be given to a pregnant woman only if clearly needed.

Pediatric Use: Safety and effectiveness have been established in the age groups infant to adolescent.

Geriatric Use: An evaluation of current literature revealed no clinical experience identifying differences in response between elderly and younger patients. In general, dose selection for an elderly patient should be cautious, usually starting at the low end of the dosing range, reflecting the greater frequency of decreased hepatic, renal, or cardiac function, and of concomitant disease or other drug therapy.

Sodium ions are known to be substantially excreted by the kidney, and the risk of toxic reactions may be greater in patients with impaired renal function. Because elderly patients are more likely to have decreased renal function, care should be taken in dose selection, and it may be useful to monitor renal function.

ADVERSE REACTIONS

Sodium overload can occur with intravenous infusion of excessive amounts of sodium-containing solutions (See WARNINGS and PRECAUTIONS).

OVERDOSAGE

In the event of overdosage, discontinue infusion containing sodium acetate immediately and institute corrective therapy as indicated to reduce elevated serum sodium levels, and restore acid-base balance if necessary (See WARNINGS, PRECAUTIONS and ADVERSE REACTIONS).

DOSAGE AND ADMINISTRATION

Sodium Acetate Injection, USP (2 mEq/mL) is administered intravenously only after dilution in a larger volume of fluid. The dose and rate of administration are dependent upon the individual needs of the patient. Serum sodium should be monitored as a guide to dosage. Using aseptic technique, transfer the desired amount to other intravenous fluids to provide the appropriate number of milliequivalents (mEq) of sodium acetate.

Sodium Acetate Injection, USP (2 mEq/mL) in the Pharmacy Bulk Package is designed for use with manual, gravity flow operations and automated compounding devices for preparing intravenous nutritional admixtures. Admixtures must be stored under refrigeration and used within 24 hours after compounding.

Parenteral drug products should be inspected visually for particulate matter and discoloration prior to administration (See PRECAUTIONS).

Directions for Dispensing From Pharmacy Bulk Package

The Pharmacy Bulk Package is for use in the Pharmacy Admixtures Service only. For hanger application, peel off the paper liner from both ends of the tape hanger to expose ¾ inch long adhesive portions. Adhere each end to the label on the bottle. The vials should be suspended as a unit in the laminar flow hood.

A single entry through the vial closure should be made with a sterile dispensing set or transfer device. Transfer individual doses to appropriate intravenous infusion solutions. Use of a syringe with needle is not recommended as it may cause leakage and multiple entries will increase the potential of microbial and particulate contamination.

The above process should be carried out under a laminar flow hood using aseptic technique. Discard any unused portion within 4 hours after initial closure entry.

HOW SUPPLIED

Sodium Acetate Injection, USP (2 mEq/mL) is supplied in Pharmacy Bulk Packages as follows:

Unit of Sale | Concentration | Each
NDC 0409-3299-26 Tray Containing 25 Units | 100 mEq/50 mL (2 mEq/mL) | NDC 0409-3299-46 Glass Fliptop Vial
NDC 0409-3299-25 Case Containing 25 Units | 200 mEq/100 mL (2 mEq/mL) | NDC 0409-3299-45 Glass Fliptop Vial

Store at 20 to 25ºC (68 to 77ºF). [See USP Controlled Room Temperature.]

Distributed by
Hospira, Inc., Lake Forest, IL 60045 USA
Novaplus is a registered trademark of Vizient, Inc.

LAB-1192-3.0

Revised: 11/2020

PRINCIPAL DISPLAY PANEL - 100 mL Vial Label

NDC 0409-3299-45
100 mL

Sodium Acetate
Injection, USP

200 mEq/100 mL (2 mEq/mL)

For Intravenous Use Only*

Pharmacy Bulk Package.
Not for Direct Infusion.

CAUTION: MUST BE DILUTED

Dist. by Hospira, Inc., Lake Forest, IL 60045 USA

novaplus™

PRINCIPAL DISPLAY PANEL - 50 mL Vial Label

NDC 0409-3299-46
50 mL

Sodium Acetate
Injection, USP

100 mEq/50 mL
(2 mEq/mL)

For Intravenous Use Only*

Pharmacy Bulk Package.
Not for Direct Infusion.

CAUTION: MUST BE DILUTED

novaplus™

PRINCIPAL DISPLAY PANEL - 50 mL Vial Tray

50 mL
Rx only
NDC 0409-3299-26
Contains 25 of NDC 0409-3299-46

Sodium Acetate Injection, USP

100 mEq/50 mL (2 mEq/mL)

For Intravenous Use Only*

Pharmacy Bulk Package. Not for Direct Infusion

novaplus™

CAUTION:
MUST BE DILUTED